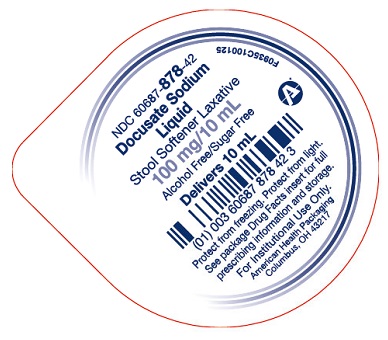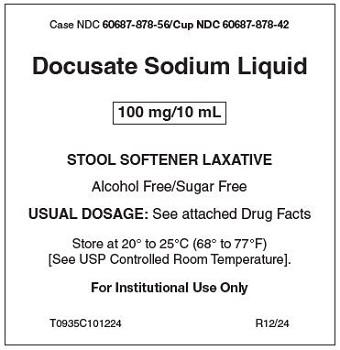 DRUG LABEL: Docusate Sodium
NDC: 60687-878 | Form: LIQUID
Manufacturer: American Health Packaging
Category: otc | Type: HUMAN OTC DRUG LABEL
Date: 20250420

ACTIVE INGREDIENTS: DOCUSATE SODIUM 100 mg/10 mL
INACTIVE INGREDIENTS: ANHYDROUS CITRIC ACID; D&C RED NO. 33; GLYCERIN; METHYLPARABEN; PROPYLENE GLYCOL; PROPYLPARABEN; WATER; SODIUM CITRATE, UNSPECIFIED FORM; SACCHARIN SODIUM; SORBITOL SOLUTION

Docusate Sodium Liquid

Active ingredient (in each 10 mL cup)

Docusate sodium 100 mg

Purpose

Stool softener

Uses

- relieves occasional constipation (irregularity)
- generally produces bowel movement in 12 to 72 hours

Warnings

Do not use

- if you are presently taking mineral oil, unless told to do so by a doctor

Ask a doctor before use if you have

- stomach pain
- nausea
- vomiting
- noticed a sudden change in bowel habits that lasts over 2 weeks

Stop use and ask a doctor if

- you have rectal bleeding or fail to have a bowel movement after use of a laxative. These could be signs of a serious condition.
- you need to use a stool softener laxative for more than 1 week
- rash occurs

If pregnant or breast-feeding,

ask a health professional before use.

Keep out of reach of children.

In case of overdose, get medical help or contact a Poison Control Center right away.

Directions:

- Dose once daily
- take with 6 to 8 oz of milk, juice or infant formula to mask the bitter taste.

adults and children 12 years and older | 5 to 20 mL (1 to 4 teaspoonfuls)
children 6 to under 12 years of age | 5 to 10 mL (1 to 2 teaspoonfuls)
children 3 to under 6 years of age | 2.5 to 5 mL (1/2 to 1 teaspoonful)
children under 3 years | ask a doctor

Other information

- Sodium content: 28 mg / 10 mL
- Store at controlled room temperature, 20° to 25°C (68° to 77°F)
- Protect from freezing
- Protect from light
- Clear pink to purple pink colored, cherry-vanilla flavored liquid supplied in the following:

10 mL unit dose cups: 100 cups (10 x 10) NDC 60687-878-56

Inactive ingredients:

artificial cherry vanilla flavoring, citric acid anhydrous, D&C Red No. 33, glycerin, methylparaben, polyethylene glycol, propylene glycol, propylparaben, purified water, saccharin sodium, sodium citrate, and sorbitol.

Questions or comments?

Call 1-800-845-8210

DO NOT USE IF SEAL IS BROKEN.

Distributed by:

American Health Packaging
Columbus, OH 43217

R12/24

Principal Display Panel – Tray Label

Case NDC 60687-878-56/Cup NDC 60687-878-42

Docusate Sodium Liquid

100 mg/10 mL

STOOL SOFTENER LAXATIVE

Alcohol Free/Sugar Free

USUAL DOSAGE: See attached Drug Facts

Store at 20° to 25°C (68° to 77°F)
[See USP Controlled Room Temperature].

For Institutional Use Only

T0935C101224 R12/24

Principal Display Panel – Cup – 100 mg / 10 mL

NDC 60687- 878-42

Docusate Sodium
Liquid

Stool Softener Laxative

100 mg/10 mL

Alcohol Free/Sugar Free

Delivers 10 mL

Protect from freezing. Protect from light.

See package Drug Facts insert for full
prescribing information and storage.

For Institutional Use Only.

American Health Packaging
Columbus, OH 43217

F0935C100125